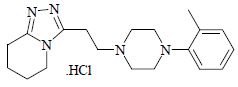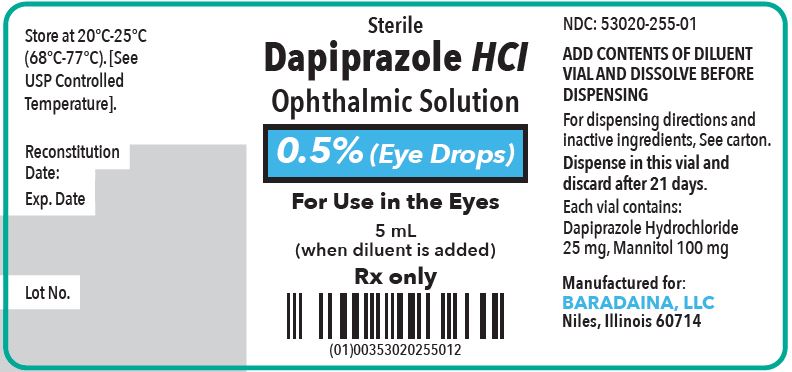 DRUG LABEL: DAPIPRAZOLE
NDC: 53020-265 | Form: KIT | Route: OPHTHALMIC
Manufacturer: Baradaina, LLC
Category: prescription | Type: HUMAN PRESCRIPTION DRUG LABEL
Date: 20240109

ACTIVE INGREDIENTS: DAPIPRAZOLE HYDROCHLORIDE 25 mg/5 mL
INACTIVE INGREDIENTS: MANNITOL; SODIUM CHLORIDE; SODIUM HYDROXIDE; HYPROMELLOSE 2208 (100 MPA.S); EDETATE SODIUM; SODIUM PHOSPHATE, DIBASIC; SODIUM PHOSPHATE, MONOBASIC, MONOHYDRATE; WATER; BENZALKONIUM CHLORIDE

Dapiprazole Hydrochloride Ophthalmic Solution, 0.5%

DESCRIPTION:

For ophthalmic use only.

Dapiprazole hydrochloride is an alpha-adrenergic blocking agent.

Dapiprazole hydrochloride is 5,6,7,8-tetrahydro-3-[2-(4- o .tolyl-1-piperazinyl)ethyl]- s -triazolo[4,3-a]pyridine hydrochloride.

Dapiprazole hydrochloride has the empirical formula C19H27N5 • HCl and a molecular weight of 361.93.

The structural formula for dapiprazole hydrochloride is:

Dapiprazole hydrochloride is a sterile, white, lyophilized powder soluble in water.

Dapiprazole hydrochloride ophthalmic solution, 0.5% is a clear, colorless, slightly viscous solution for topical application. Each mL (when reconstituted as directed) contains 5 mg of dapiprazole hydrochloride as the active ingredient.

The reconstituted solution has a pH of approximately 6.6 and an osmolarity of approximately 415 mOsm.

The inactive ingredients include: mannitol (2%), sodium chloride, hydroxypropyl methylcellulose (0.4%), edetate sodium (0.01%), sodium phosphate dibasic, sodium phosphate monobasic, water for injection, and benzalkonium chloride (0.01%) as a preservative.

Dapiprazole hydrochloride ophthalmic solution, 0.5% is supplied in a kit consisting of one vial of dapiprazole hydrochloride (25 mg), one vial of diluent (5 mL) and one dropper for dispensing.

CLINICAL PHARMACOLOGY:

Dapiprazole hydrochloride ophthalmic solution acts through blocking the alpha-adrenergic receptors in smooth muscle. Dapiprazole hydrochloride ophthalmic solution produces miosis through an effect on the dilator muscle of the iris.

Dapiprazole hydrochloride ophthalmic solution does not have any significant activity on ciliary muscle contraction and, therefore does not induce a significant change in the anterior chamber depth or the thickness of the lens.

Dapiprazole hydrochloride ophthalmic solution has demonstrated safe and rapid reversal of mydriasis produced by phenylephrine and to a lesser degree tropicamide. In patients with decreased accommodative amplitude due to treatment with tropicamide, dapiprazole hydrochloride ophthalmic solution partially restores the accommodative amplitude. This activity is not only due to its miotic effect but also to a direct effect on accommodation.

Eye color affects the rate of pupillary constriction. In individuals with brown irides, the rate of pupillary constriction may be slightly slower than in individuals with blue or green irides. Eye color does not appear to affect the final pupil size.

Dapiprazole hydrochloride ophthalmic solution does not significantly alter intraocular pressure in normotensive eyes or in eyes with elevated intraocular pressure.

INDICATIONS AND USAGE:

Dapiprazole hydrochloride ophthalmic solution is indicated in the treatment of iatrogenically induced mydriasis produced by adrenergic (phenylephrine) or parasympatholytic (tropicamide) agents. Dapiprazole hydrochloride ophthalmic solution is not indicated for the reduction of intraocular pressure or in the treatment of open angle glaucoma.

CONTRAINDICATIONS:

Miotics are contraindicated where constriction is undesirable; such as acute iritis, and in those subjects showing hypersensitivity to any component of this preparation.

WARNING:

For Topical Ophthalmic Use Only. NOT FOR INJECTION. Do not touch the dropper up to lids or any surface, as this may contaminate the solution. Dapiprazole hydrochloride ophthalmic solution should not be used in the same patient more frequently than once a week.

PRECAUTIONS:

Information to Patients:

Miosis may cause difficulty in dark adaptation and may reduce the field of vision. Patients should exercise caution when involved in night driving or other activities in poor illumination.

Carcinogenesis, Mutagenesis, Impairment of Fertility:

Dapiprazole has been shown to significantly increase the incidence of liver tumors in rats after continuous dietary administration for 104 weeks. This effect was found only in male rats treated with the highest dose administered in the study, i.e., 300 mg/kg/day, (80,000 times the human dose) and was not observed in male and female rats at doses of 30 and 100 mg/kg/day and female rats at doses of 300 mg/kg/day.

Negative results have been reported on the mutagenicity and impairment of fertility studies with dapiprazole hydrochloride.

Pregnancy:

Reproduction studies have been performed in rats and rabbits at doses up to 128,000 (rat) and 27,000 (rabbit) times the human ophthalmic dose and revealed no evidence of impaired fertility or harm to the fetus due to dapiprazole hydrochloride. There are, however, no adequate and well-controlled studies in pregnant women. Because animal reproduction studies are not always predictive of human response, this drug should be used during pregnancy only if clearly needed.

Nursing Mothers:

It is not known whether this drug is excreted in human milk. Because many drugs are excreted in human milk, caution should be exercised when dapiprazole hydrochloride ophthalmic solution is administered to a nursing woman.

Pediatric Use:

Safety and effectiveness in pediatric patients below the age of 4 have not been established.

ADVERSE REACTIONS:

In controlled studies the most frequent reaction to dapiprazole was conjunctival injection lasting 20 minutes in over 80% of patients. Burning on instillation of dapiprazole hydrochloride ophthalmic solution was reported in approximately half of all patients. Reactions occurring in 10% to 40% of patients included ptosis, lid erythema, lid edema, chemosis, itching, punctate keratitis, corneal edema, browache, photophobia and headaches. Other reactions reported less frequently included dryness of eyes, tearing and blurring of vision.

DOSAGE AND ADMINISTRATION:

Two drops followed 5 minutes later by an additional 2 drops applied topically to the conjunctiva of each eye should be administered after the ophthalmic examination to reverse the diagnostic mydriasis. Dapiprazole hydrochloride ophthalmic solution should not be used in the same patient more frequently than once per week.

Directions for Preparing Eyedrops:

1. Use aseptic technique.
2. Tear off aluminum seals, remove and discard rubber plugs from both drug and diluent vials
3. Pour diluent into drug vial.
4. Remove dropper assembly from its sterile wrapping and attach to the drug vial.
5. Shake container for several minutes to ensure mixing.

HOW SUPPLIED:

Dapiprazole hydrochloride ophthalmic solution, 0.5% - Sterile is supplied as an outer package (NDC 53020-265-01) containing:

NDC 53020-255-01 single vial of dapiprazole hydrochloride (25 mg) lyophilized powder

NDC 53020-245-01 single vial of diluent (5 mL)

Single dropper for dispensing

Storage and Stability of Eyedrops:

Once the ophthalmic solution has been reconstituted it may be stored at 20° - 25°C (68° - 77°F) [See USP Controlled Temperature] for 21 days. Discard any solution that is not clear and colorless.

Updated: February 2019

Manufactured by:
Exela Pharma Sciences, LLC
Lenoir, NC 28645

Manufactured For:
Baradaina, LLC
8780 W. Golf Road, Suite 304
Niles , Illinois 60714

Rx only

PRINCIPAL DISPLAY-Container Label

Sterile

Dapiprazole HCI

Ophthalmic Solution

0.5% E Y E D R O P S

Rx only

For Use in the Eyes
5 mL
(when diluent is added)

BARADAINA, LLC